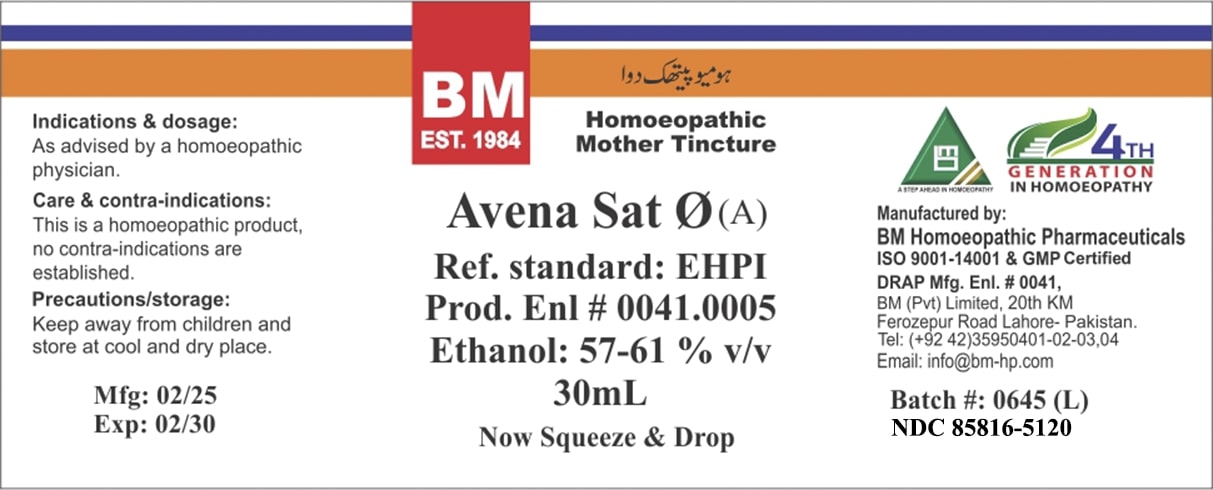 DRUG LABEL: BM Avena Sat
NDC: 85816-5120 | Form: TINCTURE
Manufacturer: BM Private Limited
Category: homeopathic | Type: HUMAN OTC DRUG LABEL
Date: 20250701

ACTIVE INGREDIENTS: AVENA SATIVA FLOWERING TOP 1 [hp_X]/1 mL
INACTIVE INGREDIENTS: ALCOHOL 0.7 mL/1 mL; WATER 0.3 mL/1 mL

BM Avena Sat Ø

Indications & dosage: As advised by a homoeopathic physician.

Indications & dosage: As advised by a homoeopathic physician.

PURPOSE

Indications & dosage: As advised by a homoeopathic physician.

CONTRAINDICATIONS

Care & contra-indications: This is a homoeopathic product, no contra-indications are established.

WARNINGS

Precautions/storage: Keep away from children and store at cool and dry place.

KEEP OUT OF REACH OF CHILDREN

Precautions/storage: Keep away from children and store at cool and dry place.

STORAGE AND HANDLING

Precautions/storage: Keep away from children and store at cool and dry place.

INACTIVE INGREDIENT

ALCOHOL, WATER

ACTIVE INGREDIENT

AVENA SATIVA

Entire package label